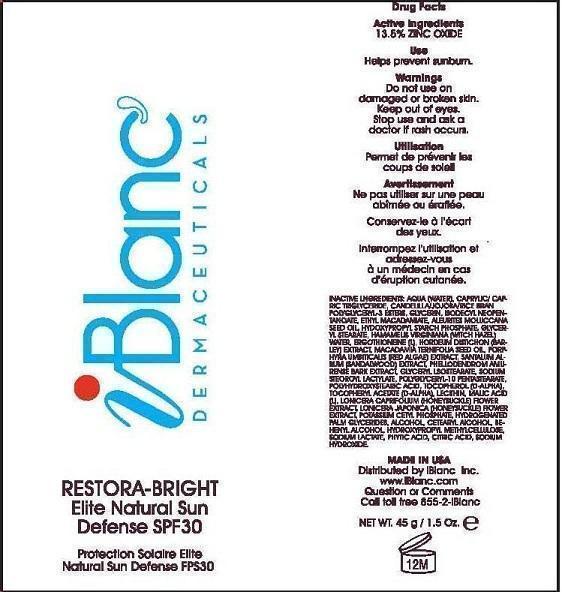 DRUG LABEL: iBlanc Restora-Bright Elite Natural Sun Defense
NDC: 52960-201 | Form: LOTION
Manufacturer: iBlanc, Inc.
Category: otc | Type: HUMAN OTC DRUG LABEL
Date: 20121026

ACTIVE INGREDIENTS: ZINC OXIDE 13.5 g/100 g
INACTIVE INGREDIENTS: WATER; CAPRYLIC/CAPRIC MONO/DIGLYCERIDES; CANDELILLA WAX; HYDROLYZED JOJOBA ESTERS (ACID FORM); RICE BRAN OIL; GLYCERIN; ISODECYL NEOPENTANOATE; ETHYL MACADAMIATE; ALEURITES MOLUCCANA SEED; HYDROXYPROPYL DISTARCH PHOSPHATE, HIGH AMYLOSE CORN; GLYCERYL MONOSTEARATE; HAMAMELIS VIRGINIANA ROOT BARK/STEM BARK; ERGOTHIONEINE; BARLEY; MACADAMIA OIL; PORPHYRA UMBILICALIS; SANDALWOOD; PHELLODENDRON AMURENSE BARK; GLYCERYL ISOSTEARATE; SODIUM STEAROYL LACTYLATE; POLYGLYCERYL-10 STEARATE; POLYHYDROXYSTEARIC ACID (2300 MW); TOCOPHEROL; .ALPHA.-TOCOPHEROL ACETATE, D-; LECITHIN, SOYBEAN; MALIC ACID, L-; LONICERA CAPRIFOLIUM FLOWER; LONICERA JAPONICA FLOWER; POTASSIUM CETYL PHOSPHATE; HYDROGENATED PALM GLYCERIDES; ALCOHOL; CETOSTEARYL ALCOHOL; DOCOSANOL; HYPROMELLOSES; SODIUM LACTATE; PHYTIC ACID; ANHYDROUS CITRIC ACID; SODIUM HYDROXIDE

ACTIVE INGREDIENT

13.5% ZINC OXIDE

PURPOSE

HELPS PREVENT SUNBURN

DO NOT USE ON DAMAGED OR BROKEN SKIN. KEEP OUT OF EYES.

KEEP OUT OF REACH OF CHILDREN.

STOP USE AND ASK A DOCTOR IF RASH OCCURS.

INACTIVE INGREDIENT

INACTIVE INGREDIENTS: AQUA (WATER), CAPRYLIC/CAPRIC TRIGLYCERIDE, CANDELILLA/JOJOBA/RICE BRAN POLYGLYCERYL-3 ESTERS, GLYCERIN, ISODECYL NEOPENTANOATE, ETHYL MACADAMIATE, ALEURITES MOLUCCANA SEED OIL, HYDROXYPROPYL STARCH PHOSPHATE, GLYCERYL STEARATE, HAMAMELIS VIRGINIANA (WITCH HAZEL) WATER, ERGOTHIONEINE (L), HORDEUM DISTICHON (BARLEY) EXTRACT, MACADAMIA TERNIFOLIA SEED OIL, PORPHYRA UMBITICALIS (RED ALGAE) EXTRACT, SANTALUM ALBUM (SANDALWOOD) EXTRACT, PHELLODENDROM AMURENSE BARK EXTRACT, GLYCERYL ISOSTEARATE, SODIUM STEROYL LACTYLATE, POLYGLYCERYL-10 PENTASTEARATE, POLYHYDROXYSTEARIC ACID, TOCOPHEROL (D-ALPHA), TOCOPHERYL ACETATE (D-ALPHA), LECITHIN, MALIC ACID (L), LONICERA CAPRIFOLIUM (HONEYSUCKLE) FLOWER EXTRACT, LONICERA JAPONICA (HONEYSUCKLE) FLOWER EXTRACT, POTASSIUM CETYL PHOSPHATE, HYDROGENATED PALM GLYCERIDES, ALCOHOL, CETEARYL ALCOHOL, BEHENYL ALCOHOL, HYDROXYPROPYL METHYLCELLULOSE, SODIUM LACTATE, PHYTIC ACID, CITRIC ACID, SODIUM HYDROXIDE.

QUESTIONS OR COMMENTS

CALL TOLL FREE 855-2-IBLANC